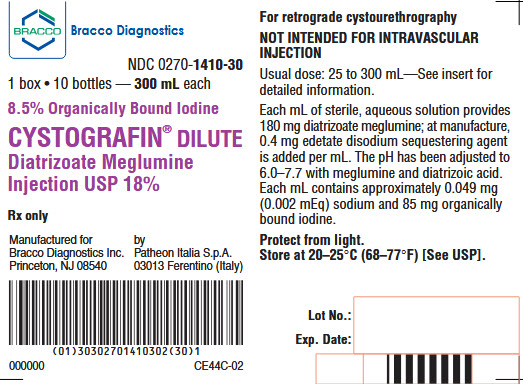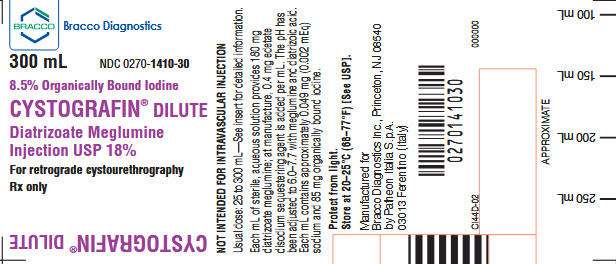 DRUG LABEL: Cystografin Dilute
NDC: 0270-1410 | Form: INJECTION, SOLUTION
Manufacturer: BRACCO DIAGNOSTICS INC
Category: prescription | Type: HUMAN PRESCRIPTION DRUG LABEL
Date: 20251123

ACTIVE INGREDIENTS: diatrizoate meglumine 180 mg/1 mL
INACTIVE INGREDIENTS: edetate disodium 0.4 mg/1 mL

CYSTOGRAFIN® DILUTE
Diatrizoate Meglumine
Injection USP 18%

For retrograde cystourethrography

Not intended for intravascular injection

DESCRIPTION

Cystografin Dilute (Diatrizoate Meglumine Injection USP 18%) is a radiopaque contrast agent supplied as a sterile, aqueous solution. Each mL provides 180 mg diatrizoate meglumine with 0.4 mg edetate disodium as a sequestering agent. Each mL of solution also contains approximately 85 mg organically bound iodine. At the time of manufacture, the air in the container is replaced by nitrogen.

INDICATION

Cystografin Dilute is indicated for retrograde cystourethrography.

CONTRAINDICATIONS

This preparation is contraindicated in patients with a hypersensitivity to salts of diatrizoic acid.

WARNINGS

Severe sensitivity reactions are more likely to occur in patients with a personaI or family history of bronchial asthma, significant allergies, or previous reactions to contrast agents.

A history of sensitivity to iodine per se or to other contrast agents is not an absolute contraindication to the use of diatrizoate meglumine, but calls for extreme caution in administration.

PRECAUTIONS

Safe and effective use of this preparation depends upon proper dosage, correct technique, adequate precautions, and readiness for emergencies.

Retrograde cystourethrography should be performed with caution in patients with a known active infectious process of the urinary tract.

Sterile technique should be employed in administration. During administration, care should be taken to avoid excessive pressure, rapid or acute distention of the bladder, and trauma.

Contrast agents may interfere with some chemical determinations made on urine specimens; therefore, urine should be collected before administration of the contrast medium or two or more days afterwards.

Pregnancy–Teratogenic Effects:

Animal reproduction studies have not been conducted with diatrizoate meglumine injection. It is also not known whether diatrizoate meglumine injection can cause fetal harm when administered to a pregnant woman or can affect reproduction capacity. Cystografin Dilute should be administered to a pregnant woman only if clearly needed.

ADVERSE REACTIONS

Retrograde genitourinary procedures may cause such complications as hematuria, perforation of the urethra or bladder, introduction of infection into the genitourinary tract, and oliguria or anuria.

If intravasation of this drug occurs, the reactions which may be associated with intravenous administration may possibly be encountered. Hypersensitivity or anaphylactoid reactions may occur. Severe reactions may be manifested by edema of the face and glottis, respiratory distress, convulsions or shock; such reactions may prove fatal unless promptly controlled by such emergency measures as maintenance of a clear airway and immediate use of oxygen and resuscitative drugs.

Endocrine: Thyroid function tests indicative of hypothyroidism or transient thyroid suppression have been uncommonly reported following iodinated contrast media administration to adult and pediatric patients, including infants. Some patients were treated for hypothyroidism.

DOSAGE AND ADMINISTRATION

Preparation of the patient: Appropriate preparation is desirable for optimal results. A laxative the night before the examination and a low residue diet the day before the procedure are recommended.

Dosage: The dose for retrograde use in cystography and voiding cystourethrography ranges from 25 to 300 mL depending on the age of the patient and the degree of bladder irritability; amounts greater than 300 mL may be used if the bladder capacity allows. Best results are obtained when the bladder is filled with the contrast agent.

Administration: After sterile catheterization, the bladder should be filled to capacity with Cystografin Dilute using a suitable sterile administration set. Care should be taken to avoid using excessive pressure. The presence of bladder discomfort or reflux and/or spontaneous voiding usually indicates that the bladder is full.

Radiography: The commonly employed radiographic techniques should be used. A scout film is recommended before the contrast agent is administered.

HOW SUPPLIED

Cystografin Dilute (Diatrizoate Meglumine Injection USP 18%) is available in packages of ten 300 mL bottIes (NDC 0270-1410-30).

Storage

Store at 20-25°C (68-77°F) [See USP]; protect from light.

Rx only

Manufactured for
Bracco Diagnostics Inc.
Princeton, NJ 08540

by Patheon Italia S.p.A.
03013 Ferentino (Italy)

Revised June 2024

PACKAGE LABEL

CYSTOGRAFIN DILUTE 18% - 300ML
NDC 0270-1410-30

CYSTOGRAFIN DILUTE 18% 1 Box - 10 BTL x 300ML
NDC 0270-1410-30